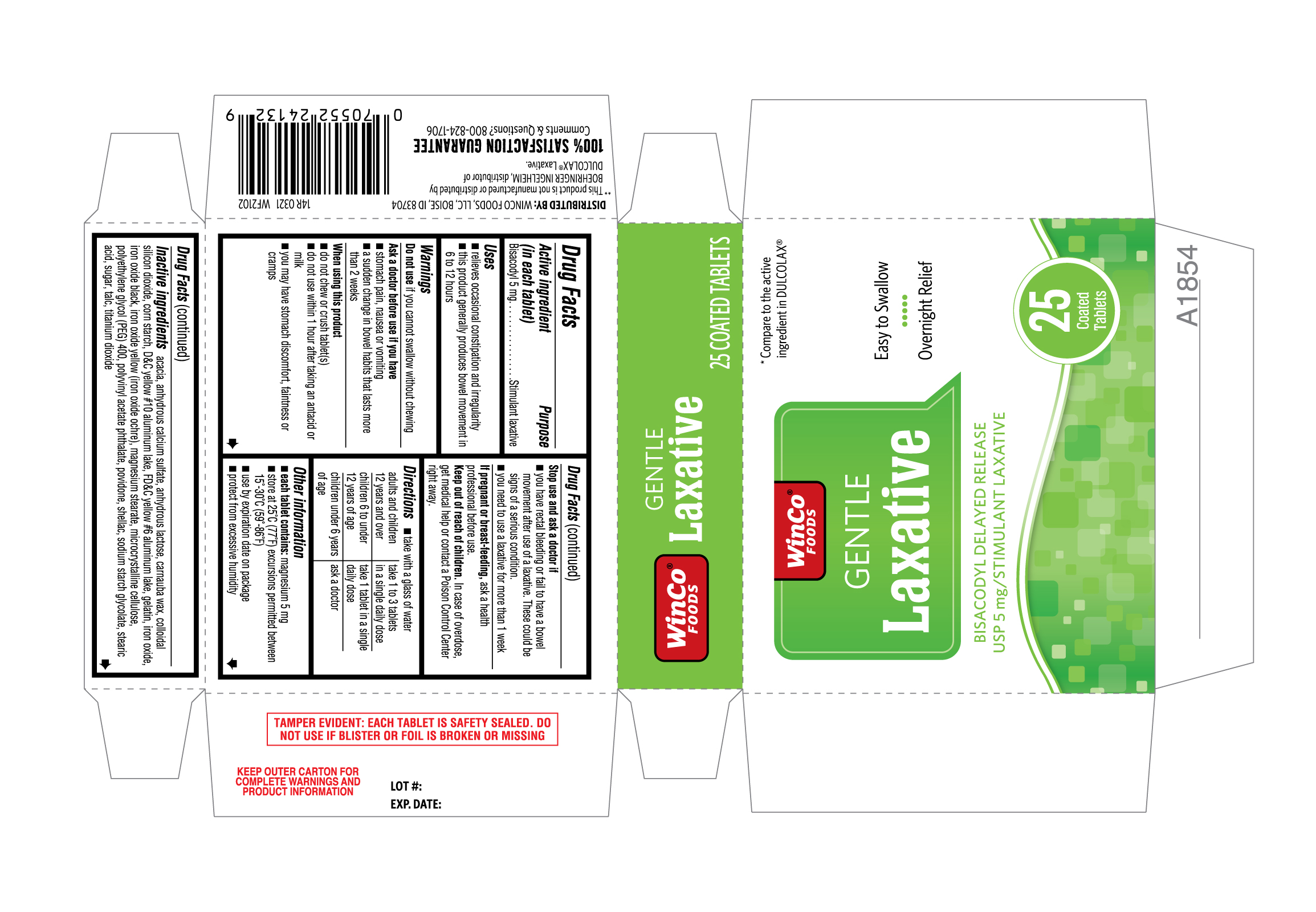 DRUG LABEL: Gentle laxative
NDC: 67091-385 | Form: TABLET
Manufacturer: WinCo Foods LLC
Category: otc | Type: HUMAN OTC DRUG LABEL
Date: 20220106

ACTIVE INGREDIENTS: BISACODYL 5 mg/1 1
INACTIVE INGREDIENTS: CARNAUBA WAX; GELATIN; SUCROSE; FERROSOFERRIC OXIDE; MAGNESIUM STEARATE; SHELLAC; ACACIA; FD&C YELLOW NO. 6; FERRIC OXIDE YELLOW; TALC; TITANIUM DIOXIDE; POLYETHYLENE GLYCOL 400; CELLULOSE, MICROCRYSTALLINE; POLYVINYL ACETATE PHTHALATE; ANHYDROUS LACTOSE; POVIDONE; SODIUM STARCH GLYCOLATE TYPE A CORN; STEARIC ACID; SILICON DIOXIDE; STARCH, CORN; D&C YELLOW NO. 10 ALUMINUM LAKE; CALCIUM SULFATE ANHYDROUS

14R Winco Foods 67091 385 Bisacodyl USP 5mg 25 count

Active ingredient (in each tablet)

Bisacodyl 5 mg

Purpose

Stimulant laxative

Uses
• relieves occasional constipation and irregularity
• this product generally produces bowel movement in 6 to 12 hours

Warnings

Do not use if you cannot swallow without chewing

Ask a doctor before use if you have
• stomach pain, nausea or vomiting
• a sudden change in bowel habits that lasts more than 2 weeks

When using this product

• do not chew or crush tablet(s)
• do not use within 1 hour after taking an antacid or milk
• you may have stomach discomfort, faintness or cramps

Stop use and ask a doctor if
• you have rectal bleeding or fail to have a bowel movement after use of a laxative. These could be signs of a serious condition.
• you need to use a laxative for more than 1 week

PREGNANCY OR BREAST FEEDING

If pregnant or breast-feeding, ask a health professional before use.

Keep out of reach of children. In case of overdose, get medical help or contact a Poison Control Center right away.

Directions

- take with a glass of water

adults and children 12 years and over | take 1 to 3 tablets in a single daily dose
children 6 to under 12 years of age | take 1 tablet in a single daily dose
children under 6 years of age | ask a doctor

Other Information
• each tablet contains: magnesium 5 mg
• store at 25°C (77°F) excursions permitted between 15°-30°C (59°-86°F)
• use by expiration date on package
• protect from excessive humidity

INACTIVE INGREDIENT

Inactive ingredients acacia, anhydrous calcium sulfate, anhydrous lactose, carnauba wax, colloidal silicon dioxide, corn starch, D&C yellow #10 aluminum lake, FD&C yellow #6 aluminum lake, gelatin, iron oxide, iron oxide black, iron oxide yellow (iron oxide ochre), magnesium stearate, microcrystalline cellulose, polyethylene glycol (PEG) 400, polyvinyl acetate phthalate, povidone, shellac, sodium starch glycolate, stearic acid, sugar, talc, titanium dioxide

Comments & Questions? 800-824-1706